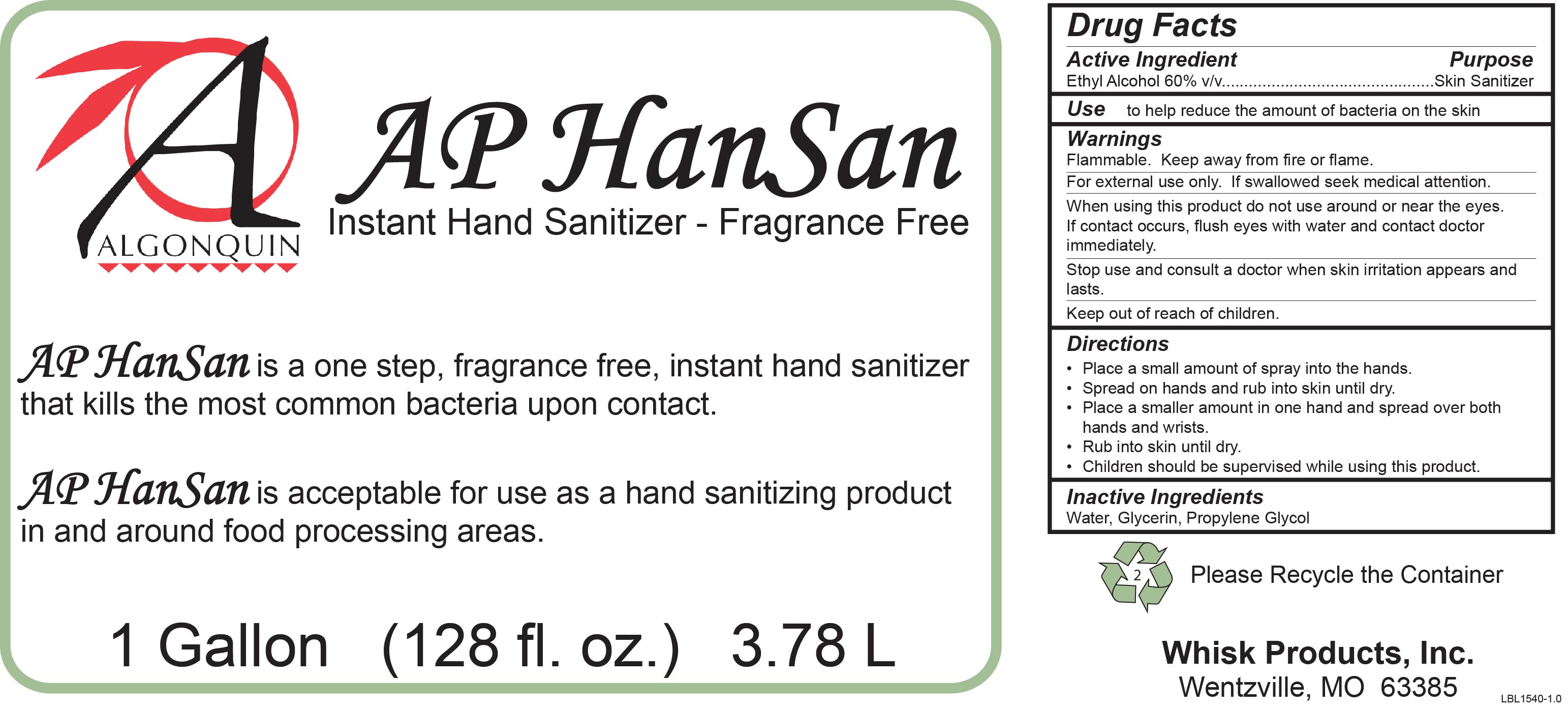 DRUG LABEL: AP HanSan
NDC: 65585-580 | Form: SPRAY
Manufacturer: WhiskProducts, Inc.
Category: otc | Type: HUMAN OTC DRUG LABEL
Date: 20231207

ACTIVE INGREDIENTS: ALCOHOL 600 mL/1 L
INACTIVE INGREDIENTS: WATER; GLYCERIN; PROPYLENE GLYCOL

AP HanSan

Active Ingredient

Ethyl Alcohol 60% v/v

Purpose

Skin Sanitizer

Use

To help reduce the amount of bacteria on the skin

Warnings

Flammable. Keep away from fire or flame.

For external use only. If swallowed seek medical attention.

When using this product do not use around or near the eyes. If contact occurs, flus eyes iwth water and contact doctor immediately.

Stop use and consult a doctor when skin irritation appears and lasts.

Keep out of reach of children.

Directions

- Place a small amount of spray into the hands.
- Spread on hands and rub into skin until dry.
- Place a smaller amount in one hand and spread over both hands and wrists.
- Rub into skin until dry.
- Children should be supervised while using this product.

Inactive Ingredients

Water, Glycerin, Propylene Glycol